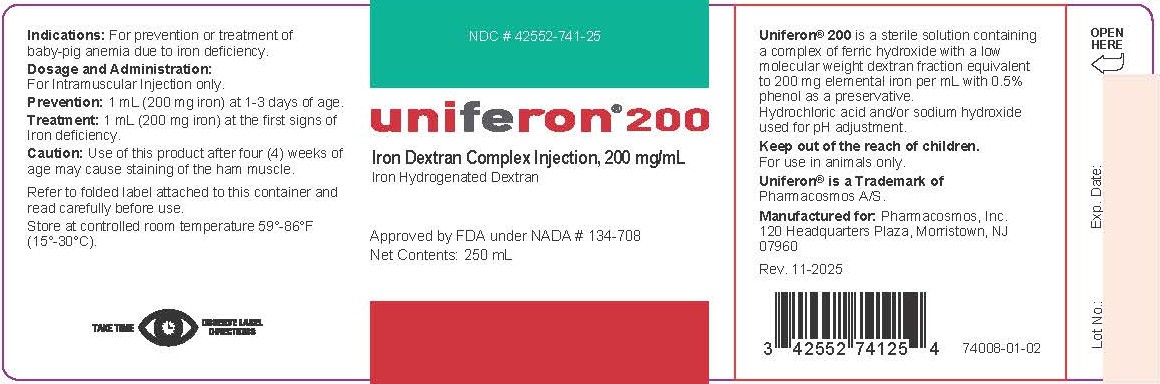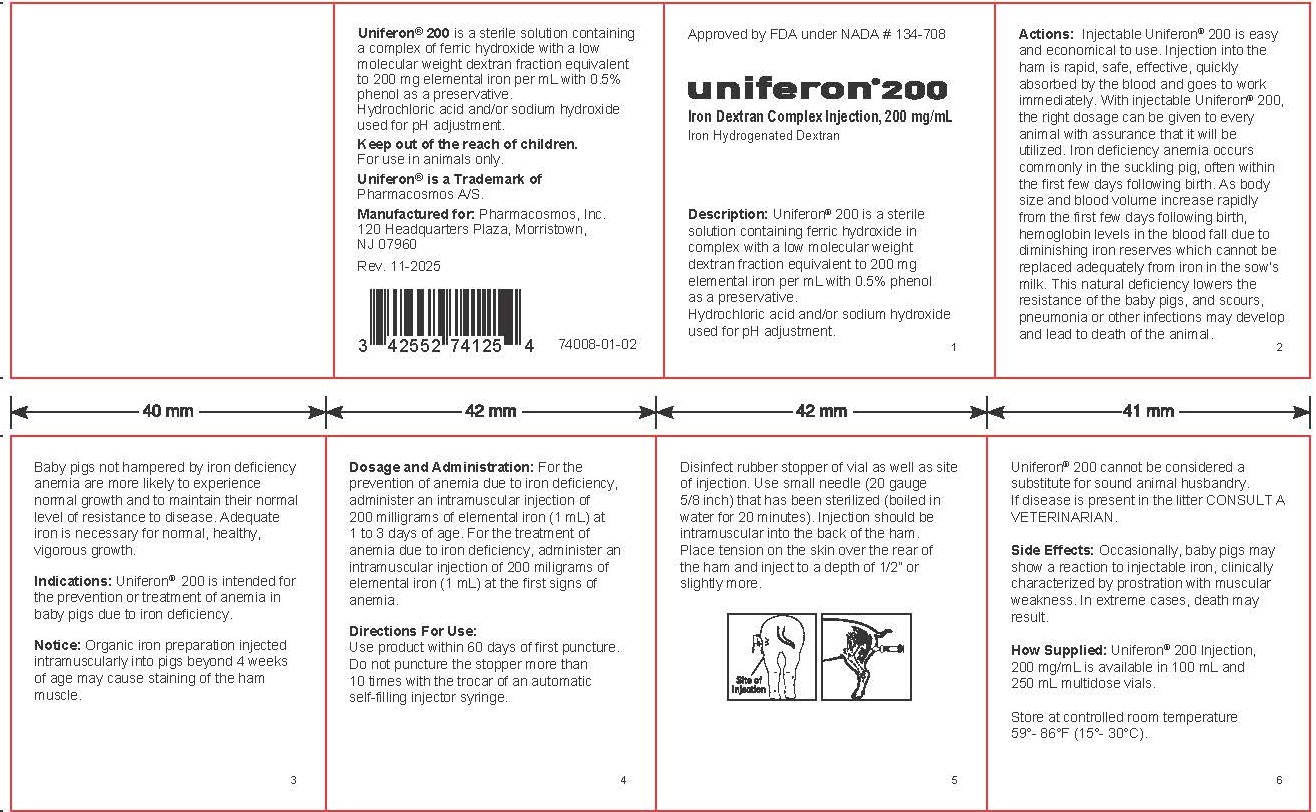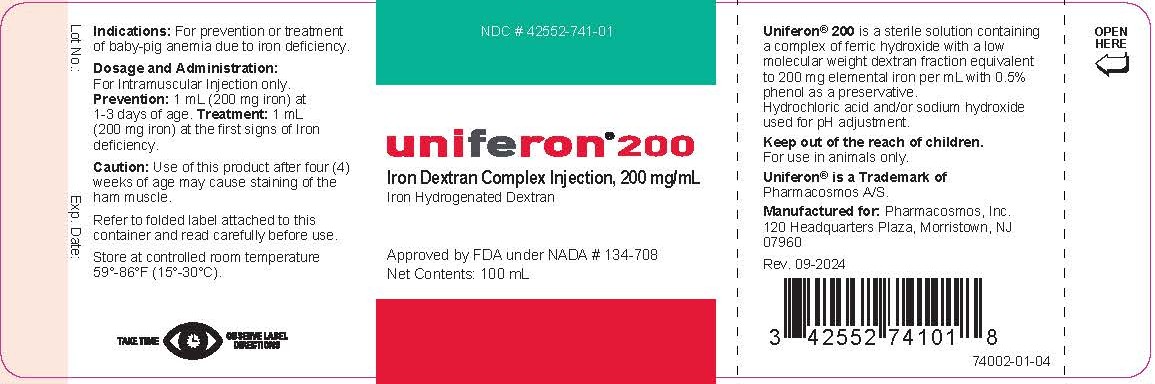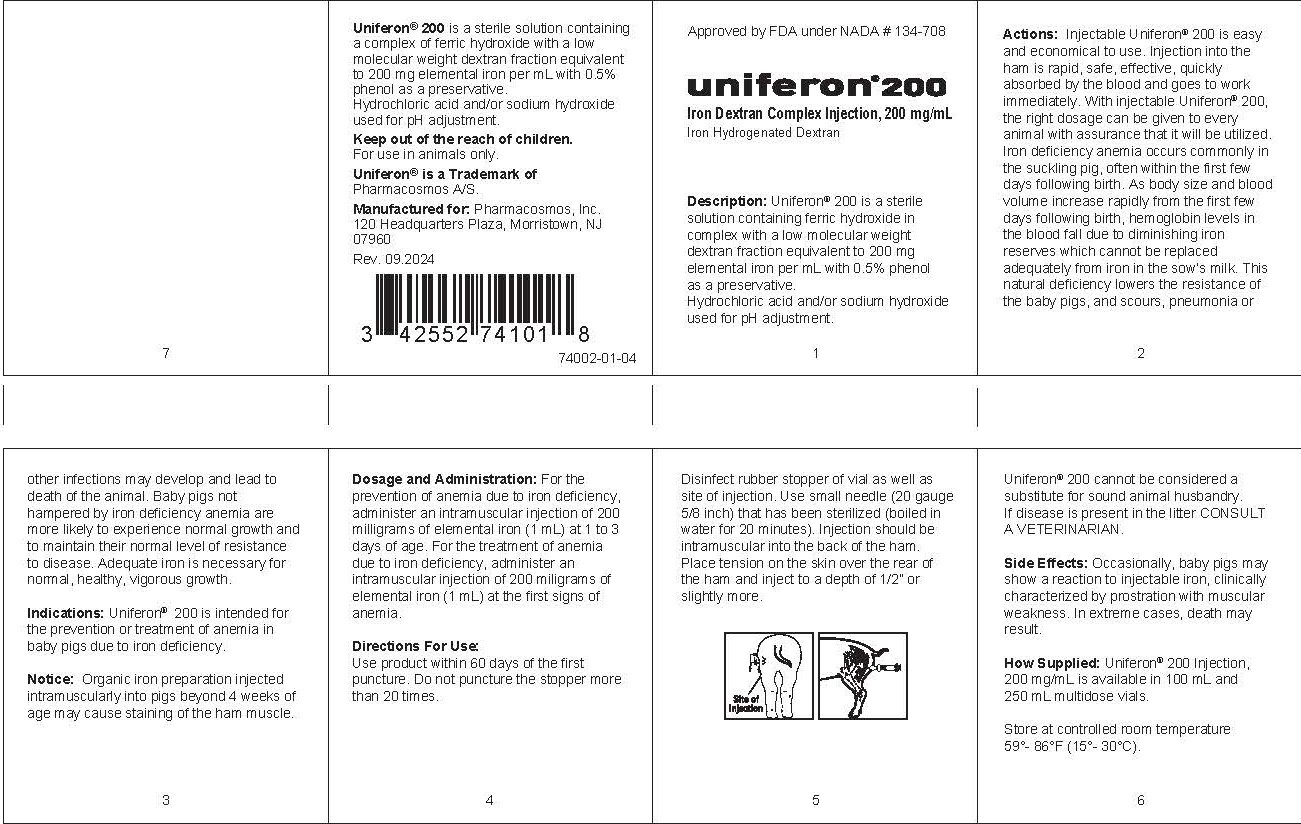 DRUG LABEL: Uniferon 200
NDC: 42552-741 | Form: INJECTION
Manufacturer: Pharmacosmos, Inc
Category: animal | Type: OTC ANIMAL DRUG LABEL
Date: 20260224

ACTIVE INGREDIENTS: IRON DEXTRAN 200 mg/1 mL
INACTIVE INGREDIENTS: PHENOL 5 mg/1 mL

Uniferon® 200

INDICATIONS AND USAGE

Indications: For prevention or treatment of baby-pig anemia due to iron deficiency.

Dosage and Administration: For Intramuscular Injection only. Prevention: 1mL (200 mg iron) at 1-3 days of age. Treatment: 1mL (200mg of iron) at the first signs of Iron deficiency

GENERAL PRECAUTIONS

Caution: Use of this product after four (4) weeks of age may cause staining of the ham muscle.

Refer to folded label attached to this container and read carefully before use.

TAKE TIME. OBSERVE LABEL DIRECTIONS

STORAGE AND HANDLING

Store at controlled room temperature 59°-86°F (15°-30°C).

Uniferon® 200 is a sterile solution containing a complex of ferric hydroxide with a low molecular weight dextran fraction equivalent to 200 mg elemental iron per mL with 0.5% phenol as a preservative. Hydrochloric acid and/or sodium hydroxide used for pH adjustment.

Uniferon® is a Trademark of Pharmacosmos A/S.

Manufactured for: Pharmacosmos, Inc., 120 Headquarters Plaza, Morristown, NJ 07960

Keep out of the reach of children.

For use in animals only.

Uniferon 200® Iron Dextran Complex Injection, 200 mg/mL

100 mL label onsert:

250 mL label onsert: